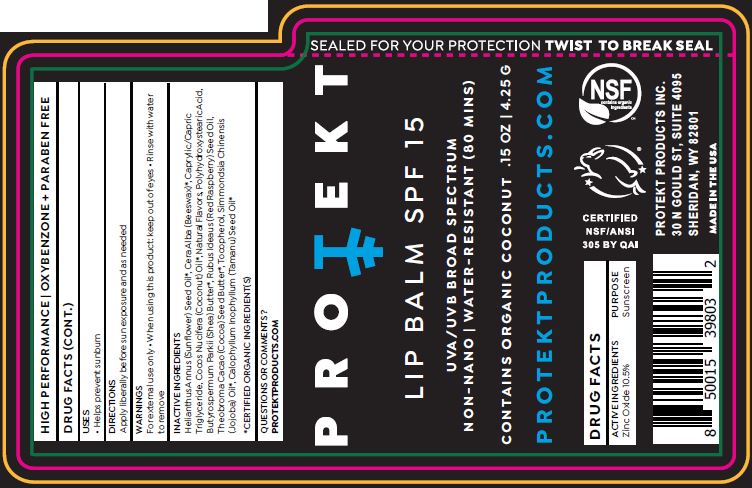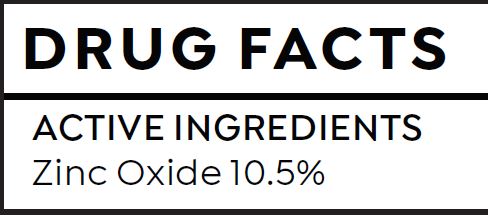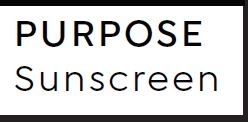 DRUG LABEL: LIP BALM
NDC: 62932-238 | Form: STICK
Manufacturer: Private Label Select Ltd CO
Category: otc | Type: HUMAN OTC DRUG LABEL
Date: 20200201

ACTIVE INGREDIENTS: ZINC OXIDE 10.5 g/100 g
INACTIVE INGREDIENTS: .DELTA.-TOCOPHEROL; POLYHYDROXYSTEARIC ACID (2300 MW); SUNFLOWER OIL; WHITE WAX; COCONUT OIL; SHEA BUTTER; MEDIUM-CHAIN TRIGLYCERIDES; JOJOBA OIL; TAMANU OIL; RASPBERRY SEED OIL; .ALPHA.-TOCOPHEROL, D-; COCOA BUTTER; POLYHYDROXYSTEARIC ACID STEARATE; .BETA.-TOCOPHEROL; .GAMMA.-TOCOPHEROL

Protekt Lip Balm SPF 15